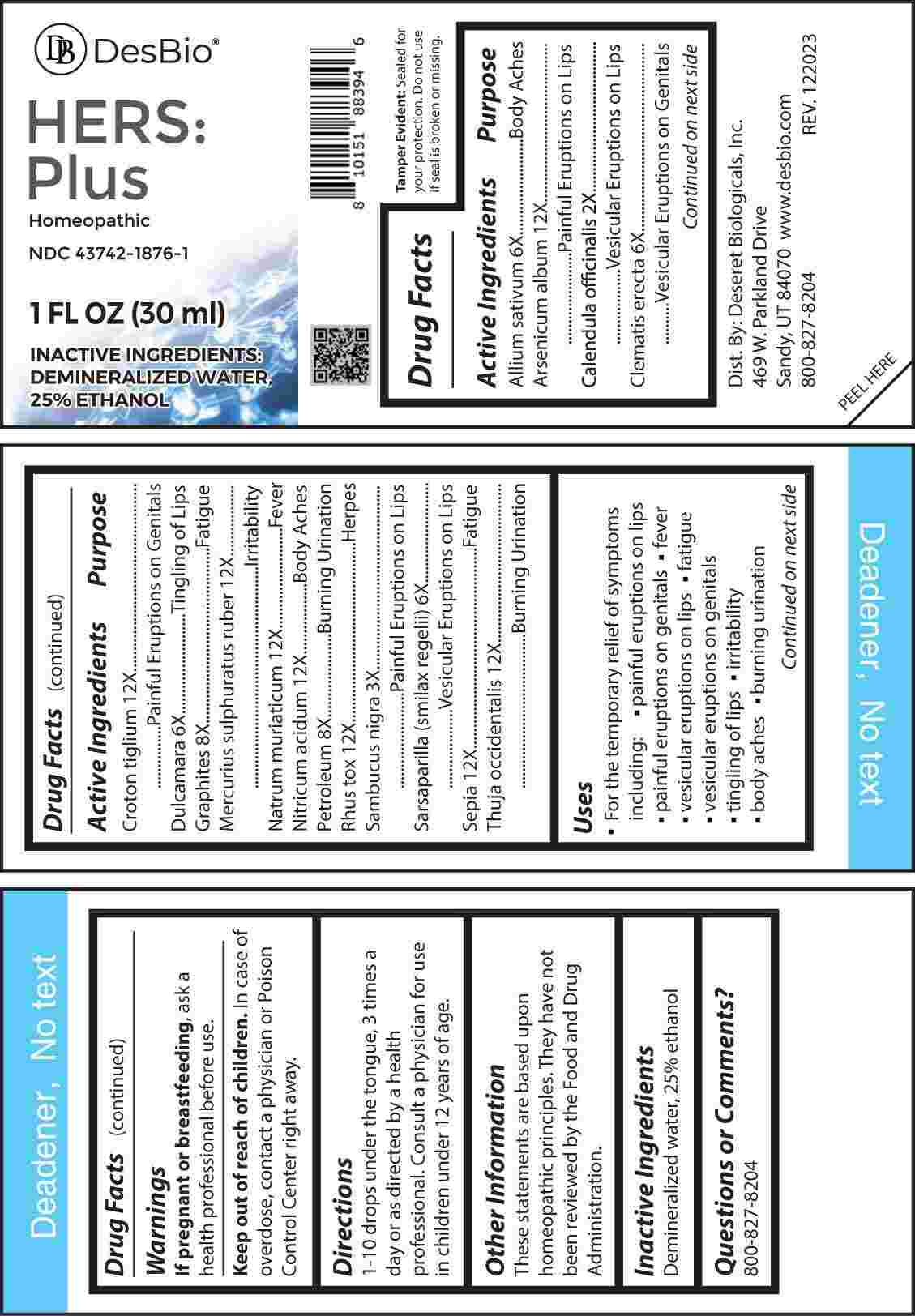 DRUG LABEL: Hers Plus
NDC: 43742-1876 | Form: LIQUID
Manufacturer: Deseret Biologicals,Inc.
Category: homeopathic | Type: HUMAN OTC DRUG LABEL
Date: 20240409

ACTIVE INGREDIENTS: CALENDULA OFFICINALIS FLOWERING TOP 2 [hp_X]/1 mL; SAMBUCUS NIGRA FLOWERING TOP 3 [hp_X]/1 mL; GARLIC 6 [hp_X]/1 mL; CLEMATIS RECTA FLOWERING TOP 6 [hp_X]/1 mL; SOLANUM DULCAMARA TOP 6 [hp_X]/1 mL; SMILAX ORNATA ROOT 6 [hp_X]/1 mL; GRAPHITE 8 [hp_X]/1 mL; KEROSENE 8 [hp_X]/1 mL; ARSENIC TRIOXIDE 12 [hp_X]/1 mL; CROTON TIGLIUM SEED 12 [hp_X]/1 mL; MERCURIC SULFIDE 12 [hp_X]/1 mL; SODIUM CHLORIDE 12 [hp_X]/1 mL; NITRIC ACID 12 [hp_X]/1 mL; TOXICODENDRON PUBESCENS LEAF 12 [hp_X]/1 mL; SEPIA OFFICINALIS JUICE 12 [hp_X]/1 mL; THUJA OCCIDENTALIS LEAFY TWIG 12 [hp_X]/1 mL
INACTIVE INGREDIENTS: WATER; ALCOHOL

DRUG FACTS:

ACTIVE INGREDIENTS:

Allium Sativum 6X, Arsenicum Album 12X, Calendula Officinalis 2X, Clematis Erecta 6X, Croton Tiglium 12X, Dulcamara 6X, Graphites 8X, Mercurius Sulphuratus Ruber 12X, Natrum Muriaticum 12X, Nitricum Acidum 12X, Petroleum 8X, Rhus Tox 12X, Sambucus Nigra 3X, Sarsaparilla (Smilax Regelii) 6X, Sepia 12X, Thuja Occidentalis 12X.

PURPOSE:

Allium Sativum – Body Aches, Arsenicum Album – Painful Eruptions on Lips, Calendula Officinalis – Vesicular Eruptions on Lips, Clematis Erecta – Vesicular Eruptions on Genitals, Croton Tiglium – Painful Eruptions on Genitals, Dulcamara – Tingling of Lips, Graphites - Fatigue, Mercurius Sulphuratus Ruber - Irritability, Natrum Muriaticum - Fever, Nitricum Acidum – Body Aches, Petroleum – Burning Urination, Rhus Tox - Herpes, Sambucus Nigra – Painful Eruptions on Lips, Sarsaparilla (Smilax Regelii) – Vesicular Eruptions on Lips, Sepia - Fatigue, Thuja Occidentalis – Burning Urination

USES:

• For the temporary relief of symptoms including:

• painful eruptions of lips • painful eruptions on genitals

• fever • vesicular eruptions on lips • fatigue

• vesicular eruptions on genitals • tingling of lips

• irritability • body aches • burning urination

These statements are based upon homeopathic principles. They have not been reviewed by the Food and Drug Administration.

WARNING:

If pregnant or breast-feeding, ask a health professional before use.

Keep out of reach of children. In case of overdose, contact a physician or Poison Control Center right away.

Tamper Evident: Sealed for your protection. Do not use if seal is broken or missing.

KEEP OUT OF REACH OF CHILDREN:

In case of overdose, contact a physician or Poison Control Center right away.

DIRECTIONS:

1-10 drops under the tongue, 3 times a day or as directed by a health professional. Consult a physician for use in children under 12 years of age.

INACTIVE INGREDIENTS:

Demineralized water, 25% ethanol

QUESTIONS:

Dist. By: Deseret Biologicals, Inc.

469 W. Parkland Drive

Sandy, UT 84070

www.desbio.com

800-827-8204

PACKAGE LABEL DISPLAY:

Des Bio

HERS:Plus

Homeopathic

NDC 43742-1876-1

1 FL OZ (30 ml)